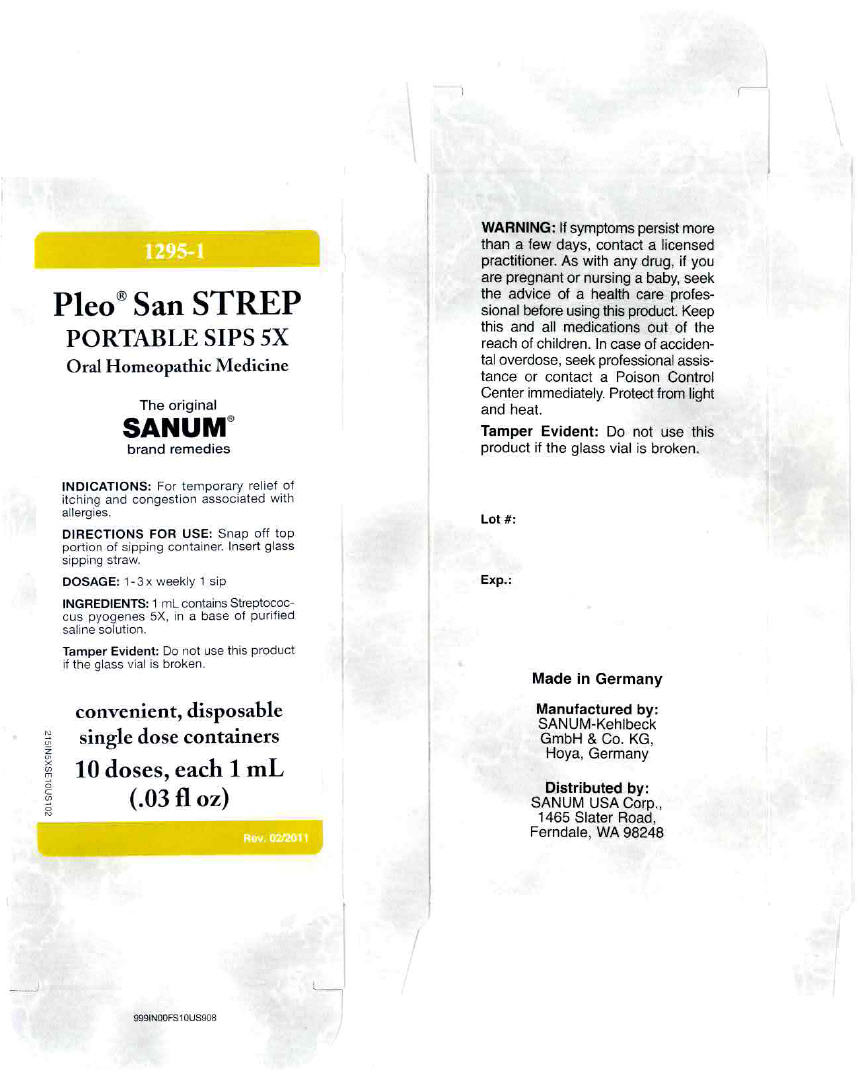 DRUG LABEL: Pleo San Strep
NDC: 60681-1295 | Form: LIQUID
Manufacturer: Sanum Kehlbeck GmbH & Co. KG
Category: homeopathic | Type: HUMAN OTC DRUG LABEL
Date: 20111111

ACTIVE INGREDIENTS: streptococcus pyogenes 5 [hp_X]/1 mL
INACTIVE INGREDIENTS: water; sodium chloride

Pleo® San STREP
PORTABLE SIPS 5X

PURPOSE

Oral Homeopathic Medicine

10 doses, each 1 mL
(.03 fl oz)

INDICATIONS

For temporary relief of itching and congestion associated with allergies.

DIRECTIONS FOR USE

Snap off top portion of sipping container. Insert glass sipping straw.

DOSAGE

1-3 x weekly 1 sip

INGREDIENTS

INACTIVE INGREDIENT

1 mL contains Streptococcus pyogenes 5X, in a base of purified saline solution.

WARNING

If symptoms persist more than a few days, contact a licensed practitioner. As with any drug, if you are pregnant or nursing a baby, seek the advice of a health care professional before using this product.

KEEP OUT OF REACH OF CHILDREN

Keep this and all medications out of the reach of children. In case of accidental overdose, seek professional assistance or contact a Poison Control Center immediately.

STORAGE AND HANDLING

Protect from light and heat.

Tamper Evident

Do not use this product if the glass vial is broken.

Made in Germany

Manufactured by:
SANUM-Kehlbeck
GmbH & Co. KG,
Hoya, Germany

Distributed by:
SANUM USA Corp.,
1465 Slater Road,
Ferndale, WA 98248

Rev. 02/2011

PRINCIPAL DISPLAY PANEL - 1 mL Vial Carton

1295-1

Pleo® San STREP
PORTABLE SIPS 5X

Oral Homeopathic Medicine

The original
SANUM®
brand remedies

INDICATIONS: For temporary relief of
itching and congestion associated with
allergies.

DIRECTIONS FOR USE: Snap off top
portion of sipping container. Insert glass
sipping straw.

DOSAGE: 1-3 x weekly 1 sip

INGREDIENTS: 1 mL contains Streptococ-
cus pyogenes 5X, in a base of purified
saline solution.

Tamper Evident: Do not use this product
if the glass vial is broken.

convenient, disposable
single dose containers

10 doses, each 1 mL
(.03 fl oz)

Rev. 02/2011

215IN5XSE10US102